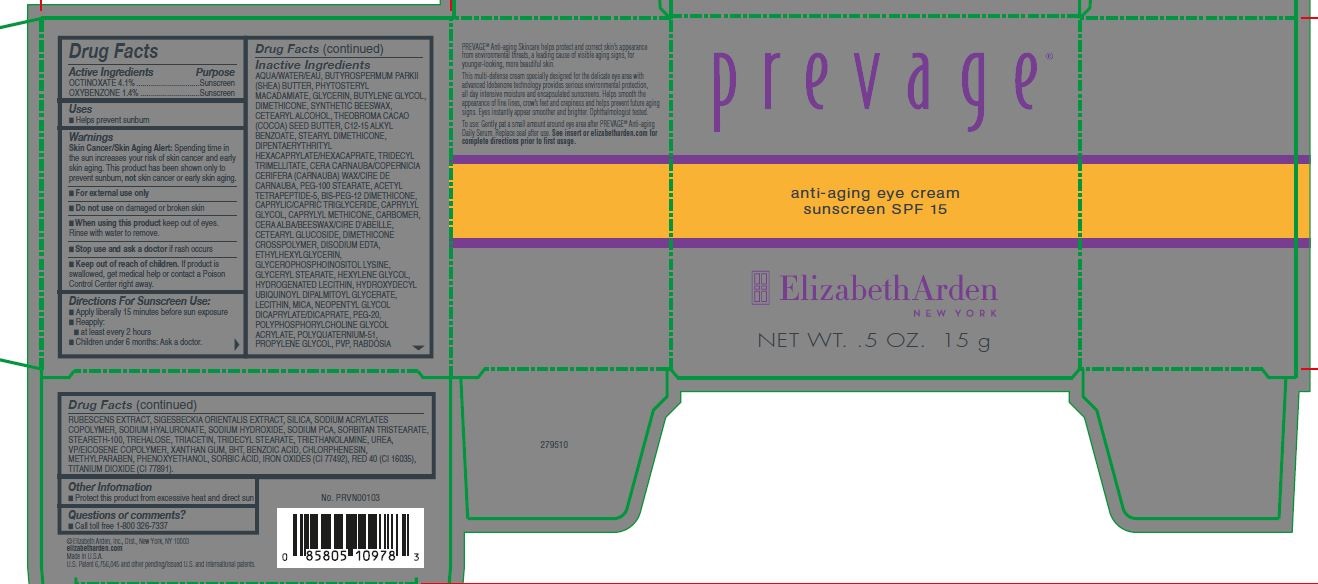 DRUG LABEL: Prevage Anti-aging eye cream SPF 15
NDC: 10967-685 | Form: CREAM
Manufacturer: Revlon
Category: otc | Type: HUMAN OTC DRUG LABEL
Date: 20251229

ACTIVE INGREDIENTS: OXYBENZONE 1.4 mg/1 g; OCTINOXATE 4.1 mg/1 g
INACTIVE INGREDIENTS: CARBOMER HOMOPOLYMER, UNSPECIFIED TYPE; HYDROGENATED SOYBEAN LECITHIN; CETOSTEARYL ALCOHOL; SODIUM PYRROLIDONE CARBOXYLATE; STEARETH-100; MEDIUM-CHAIN TRIGLYCERIDES; PEG-100 STEARATE; GLYCEROPHOSPHOINOSITOL LYSINE; SORBITAN TRISTEARATE; TITANIUM DIOXIDE; CARNAUBA WAX; CAPRYLYL TRISILOXANE; HYDROXYDECYL UBIQUINOYL DIPALMITOYL GLYCERATE; BUTYLENE GLYCOL; COCOA BUTTER; STEARYL DIMETHICONE (400 MPA.S AT 50C); MICA; TRIDECYL STEARATE; EDETATE DISODIUM ANHYDROUS; PROPYLENE GLYCOL; SIGESBECKIA ORIENTALIS WHOLE; FERRIC OXIDE YELLOW; SYNTHETIC BEESWAX; FD&C RED NO. 40; ISODON RUBESCENS WHOLE; DIMETHICONE 1000; CAPRYLYL GLYCOL; TRIDECYL TRIMELLITATE; SORBIC ACID; POLYQUATERNIUM-51 (2-METHACRYLOYLOXYETHYL PHOSPHORYLCHOLINE/N-BUTYL METHACRYLATE; 3:7); HEXYLENE GLYCOL; NEOPENTYL GLYCOL DICAPRYLATE/DICAPRATE; POLYETHYLENE GLYCOL 1000; TREHALOSE; TROLAMINE; WATER; UREA; XANTHAN GUM; GLYCERIN; BENZOIC ACID; CHLORPHENESIN; METHYLPARABEN; PEG-9 DIGLYCIDYL ETHER/SODIUM HYALURONATE CROSSPOLYMER; SODIUM HYDROXIDE; PHENOXYETHANOL; BIS-PEG-12 DIMETHICONE (70 MPA.S); TRIACETIN; ETHYLHEXYLGLYCERIN; LECITHIN, SOYBEAN; BUTYROSPERMUM PARKII (SHEA) BUTTER UNSAPONIFIABLES; PHYTOSTERYL MACADAMIATE; CETEARYL GLUCOSIDE; POVIDONE; DIMETHICONE CROSSPOLYMER (450000 MPA.S AT 12% IN CYCLOPENTASILOXANE); BUTYL ACRYLATE/METHYL METHACRYLATE/METHACRYLIC ACID COPOLYMER (18000 MW); GLYCERYL MONOSTEARATE; SILICON DIOXIDE; VINYLPYRROLIDONE/EICOSENE COPOLYMER; BUTYLATED HYDROXYTOLUENE; ALKYL (C12-15) BENZOATE; YELLOW WAX

Prevage Anti-aging eye cream SPF 15

Active Ingredient

Octinoxate 4.1 %

Oxybenzone 1.4 %

When using this product keep out of eyes. Rinse with water to remove.

Uses

Helps proevent sunburn

Keep out of reach of children. If product is swallowed, get medical help or contact a Poison Control Center right away.

WARNINGS AND PRECAUTIONS

- Skin Cancer/Skin Aging Alert: Spending time in the sun inceases your risk of ksin cancer and easly skin aging. his product has been shown only to proevent subbrun, not skin cancer or early skin aging.

- For external use only

- Do not use on danaged or broken skin

- Stop using and ask a doctor if rash occurs

Directions for Sunscreen Use:

-Apply liberally 15 minutes before sun exposure

-Repply: at least every 2 hours

Children under 6 months: Ask a doctor

INACTIVE INGREDIENT

WATER/AQUA/EAU, BUTYROSPERMUM PARKII (SHEA) BUTTER, PHYTOSTERYL MACADAMIATE, BUTYLENE GLYCOL, GLYCERIN, DIMETHICONE, SYNTHETIC BEESWAX, CETEARYL ALCOHOL, THEOBROMA CACAO (COCOA) SEED BUTTER, C12-15 ALKYL BENZOATE, STEARYL DIMETHICONE, DIPENTAERYTHRITYL HEXACAPRYLATE/HEXACAPRATE, TRIDECYL TRIMELLITATE, COPERNICIA CERIFERA (CARNAUBA) WAX/CERA CARNAUBA/CIRE DE CARNAUBA, PEG-100 STEARATE, ACETYL TETRAPEPTIDE-5, BEESWAX/CERA ALBA/CIRE D'ABEILLE, BIS-PEG-12 DIMETHICONE, CAPRYLIC/CAPRIC TRIGLYCERIDE, CAPRYLYL GLYCOL, CAPRYLYL METHICONE, CARBOMER, CETEARYL GLUCOSIDE, DIMETHICONE CROSSPOLYMER, DISODIUM EDTA, ETHYLHEXYLGLYCERIN, GLYCEROPHOSPHOINOSITOL LYSINE, GLYCERYL STEARATE, HEXYLENE GLYCOL, HYDROGENATED LECITHIN, HYDROXYDECYL UBIQUINOYL DIPALMITOYL GLYCERATE, LECITHIN, MICA, NEOPENTYL GLYCOL DICAPRYLATE/DICAPRATE, PEG-20, POLYPHOSPHORYLCHOLINE GLYCOL ACRYLATE, POLYQUATERNIUM-51, PROPYLENE GLYCOL, PVP, RABDOSIA RUBESCENS EXTRACT, SIGESBECKIA ORIENTALIS EXTRACT, SILICA, SODIUM ACRYLATES COPOLYMER, SODIUM CITRATE, SODIUM HYALURONATE, SODIUM HYDROXIDE, SODIUM PCA, SORBITAN TRISTEARATE, STEARETH-100, TREHALOSE, TRIDECYL STEARATE, UREA, VP/EICOSENE COPOLYMER, XANTHAN GUM, BHT, BENZOIC ACID, CETRIMONIUM CHLORIDE, CHLORPHENESIN, DIAZOLIDINYL UREA, METHYLPARABEN, PHENOXYETHANOL, PROPYLPARABEN, SORBIC ACID, TRIACETIN, IRON OXIDES (CI 77492), RED 40 (CI 16035), TITANIUM DIOXIDE (CI 77891).

INDICATIONS AND USAGE

- Helps prevent sunburn
- If used as directed with other sun protection measures (see Directions), decreases the risk of skin cancer and early skin againg caused by the sun

WARNINGS

- For external use only.
- Do not use on damaged or broken skin.
- When using this product keep out of eyes. Rinse with water to remove.
- Stop using and ask a doctor if rash occurs.